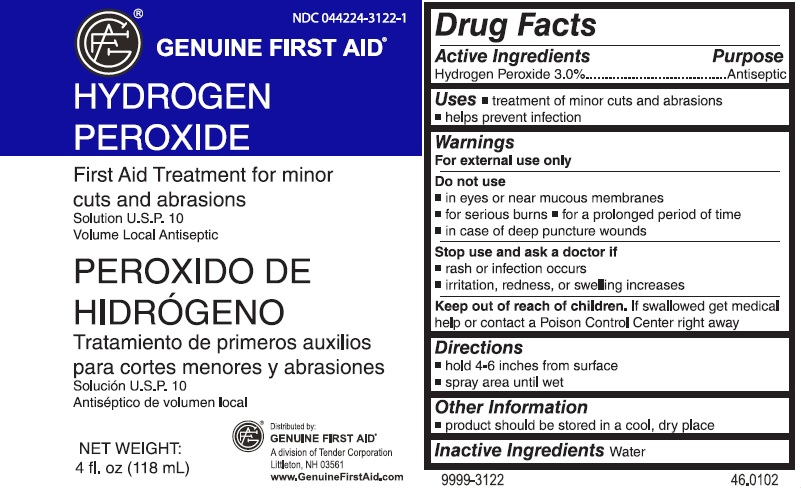 DRUG LABEL: Hydrogen Peroxide
NDC: 44224-3122 | Form: SPRAY
Manufacturer: Tender Corporation
Category: otc | Type: HUMAN OTC DRUG LABEL
Date: 20160621

ACTIVE INGREDIENTS: HYDROGEN PEROXIDE 3.57 mL/118 mL
INACTIVE INGREDIENTS: WATER

Genuine First Aid Hydrogen Peroxide

ACTIVE INGREDIENTS

Hydrogen Peroxide 3.0%

PURPOSE

Topical Antiseptic

USES

- treatment of minor cuts and abrasions
- helps prevent infection

Warnings

For external use only

Do not use

- in eyes or near mucous membranes
- for serious burns
- for a prolonged period of time
- in case of deep puncture wounds

Stop use and ask a doctor if

- rash or infection occurs
- irritation, redness, or swelling increases

Keep out of reach of children.

If swallowed get medical help or contact a Poison Control Center right away

Directions

- hold 4-6 inches from surface
- spray area until wet

Other Information

- product should be stored in a cool, dry place

Inactive Ingredients

Water